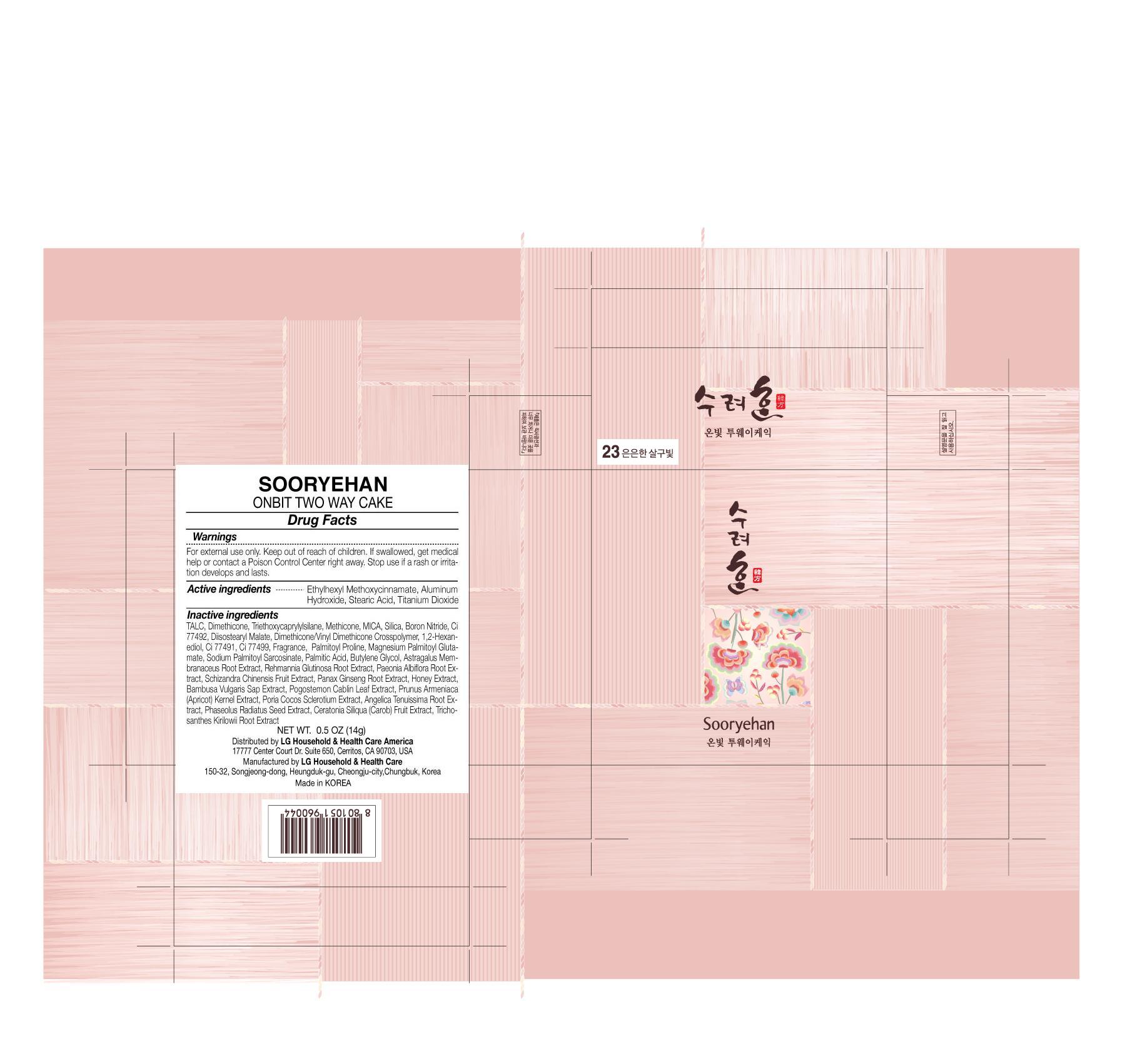 DRUG LABEL: Soorhyehan Onbit Two Way Cake 23
NDC: 53208-545 | Form: POWDER
Manufacturer: LG Household and Healthcare, Inc.
Category: otc | Type: HUMAN OTC DRUG LABEL
Date: 20110825

ACTIVE INGREDIENTS: TITANIUM DIOXIDE 5.88 g/100 g; OCTINOXATE 4 g/100 g
INACTIVE INGREDIENTS: TALC; DIMETHICONE; TRIETHOXYCAPRYLYLSILANE; MICA; TRICHOSANTHES KIRILOWII ROOT; SILICON DIOXIDE; BORON NITRIDE; FERRIC OXIDE YELLOW; 1,2-HEXANEDIOL; FERRIC OXIDE RED; FERROSOFERRIC OXIDE; CAROB; PALMITIC ACID; BUTYLENE GLYCOL; ASTRAGALUS PROPINQUUS ROOT; REHMANNIA GLUTINOSA ROOT; PAEONIA LACTIFLORA ROOT; SCHISANDRA CHINENSIS FRUIT; ASIAN GINSENG; HONEY; BAMBUSA VULGARIS SAP; PATCHOULI OIL; PRUNUS ARMENIACA SEED; LIGUSTICUM TENUISSIMUM ROOT

Soorhyehan Onbit Two Way Cake 23

ACTIVE INGREDIENT

TITANIUM DIOXIDE 5.88g/100g

OCTINOXATE 4g/100g

WARNINGS AND PRECAUTIONS

For external use only

Keep out of reach of children. Is swallowed, get medical help or contact a Poison Control Center right away.

WHEN USING

Keep out of eyes. Rinse with water to remove.

Stop use if a rash or irritation develops and lasts.

PACKAGE LABEL

ONBIT TWO WAY CAKE 23